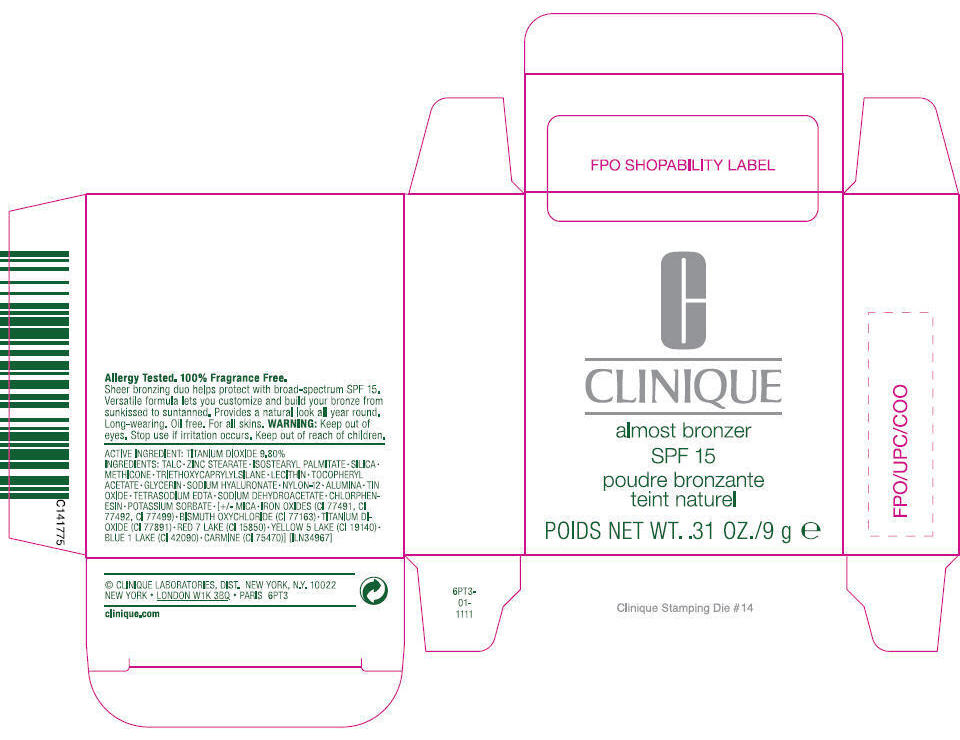 DRUG LABEL: almost bronzer 
NDC: 49527-801 | Form: POWDER
Manufacturer: clinique laboratories inc
Category: otc | Type: HUMAN OTC DRUG LABEL
Date: 20110818

ACTIVE INGREDIENTS: titanium dioxide 9.8 g/100 g
INACTIVE INGREDIENTS: talc; zinc stearate; silicon dioxide; triethoxycaprylylsilane; glycerin; hyaluronate sodium; stannic oxide; edetate sodium; sodium dehydroacetate; chlorphenesin; potassium sorbate; ferric oxide red; ferric oxide yellow; ferrosoferric oxide; bismuth oxychloride; cochineal; D&C red no. 7; FD&C yellow no. 5; FD&C blue no. 1; aluminum oxide; lecithin, soybean; mica; alpha-tocopherol acetate

CLINIQUE
almost bronzer
SPF 15

WARNING

WHEN USING

Keep out of eyes.

Stop use if irritation occurs.

Keep out of reach of children.

ACTIVE INGREDIENT

TITANIUM DIOXIDE 9.80%

INGREDIENTS

TALC • ZINC STEARATE • ISOSTEARYL PALMITATE • SILICA • METHICONE • TRIETHOXYCAPRYLYLSILANE • LECITHIN • TOCOPHERYL ACETATE • GLYCERIN • SODIUM HYALURONATE • NYLON-12 • ALUMINA • TIN OXIDE • TETRASODIUM EDTA • SODIUM DEHYDROACETATE • CHLORPHENESIN • POTASSIUM SORBATE • [+/- MICA • IRON OXIDES (CI 77491 • CI 77492 • CI 77499) • BISMUTH OXYCHLORIDE (CI 77163) • TITANIUM DIOXIDE (CI 77891) • RED 7 LAKE (CI 15850) • YELLOW 5 LAKE (CI 19140) • BLUE 1 LAKE (CI 42090) • CARMINE (CI 75470)] [ILN34967]

© CLINIQUE LABORTORIES, DIST. NEW YORK, N.Y. 10022

PRINCIPAL DISPLAY PANEL - 9g Carton

C
CLINIQUE

almost bronzer
SPF 15
poudre bronzante
teint naturel

POIDS NET WT. .31 OZ./9 g e